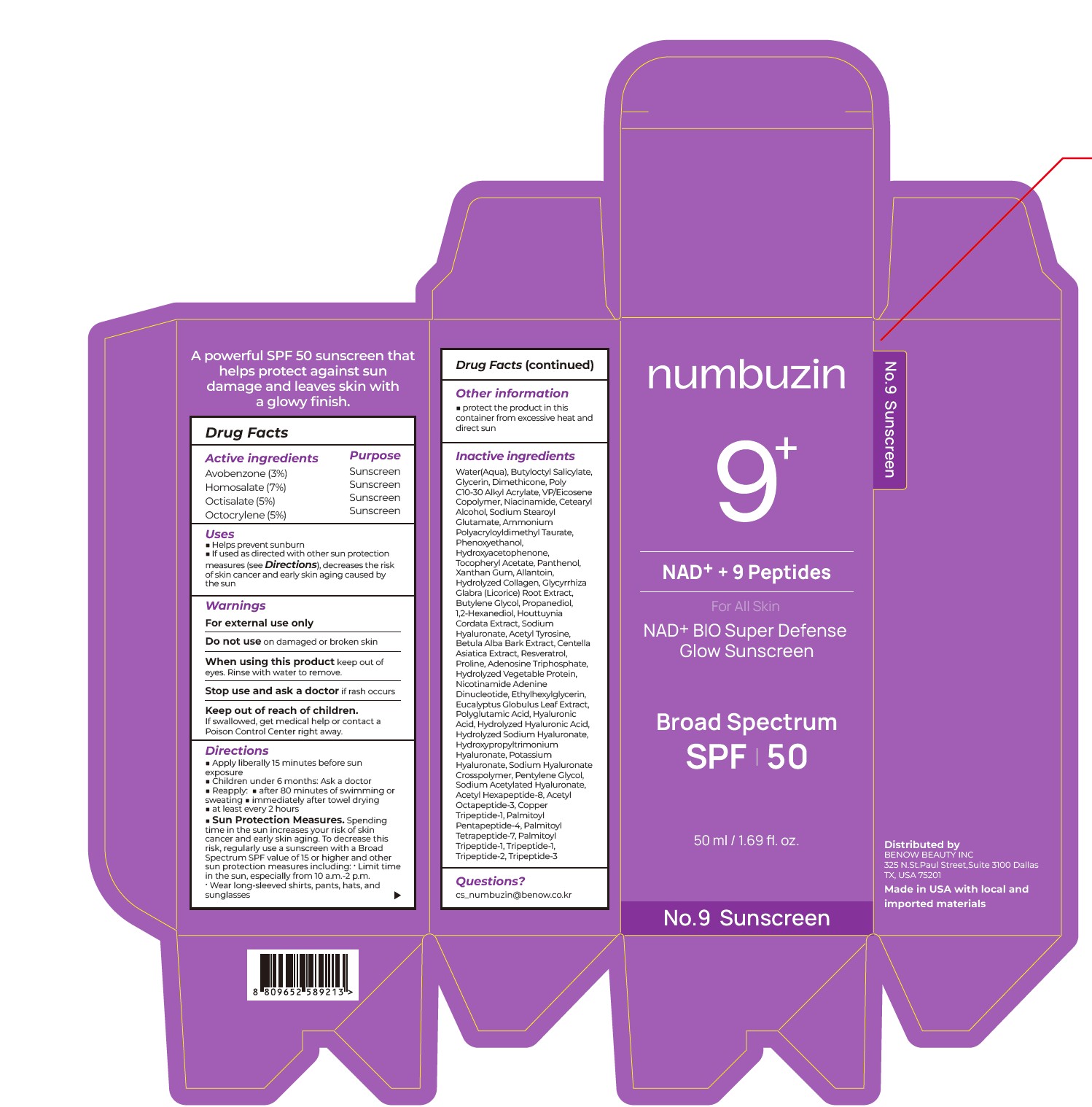 DRUG LABEL: numbuzin 9 NAD BIO Super Defense Glow Sunscreen Broad Spectrum SPF 50
NDC: 85550-001 | Form: CREAM
Manufacturer: BENOW BEAUTY INC
Category: otc | Type: HUMAN OTC DRUG LABEL
Date: 20260209

ACTIVE INGREDIENTS: HOMOSALATE 7 g/100 mL; OCTISALATE 5 g/100 mL; AVOBENZONE 3 g/100 mL; OCTOCRYLENE 5 g/100 mL
INACTIVE INGREDIENTS: PALMITOYL TETRAPEPTIDE-7; TRIPEPTIDE-1; GLYCYRRHIZA GLABRA (LICORICE) ROOT; DIMETHICONE; PANTHENOL; ALLANTOIN; NICOTINAMIDE ADENINE DINUCLEOTIDE; ACETYL OCTAPEPTIDE-3; COPPER TRIPEPTIDE-1; PALMITOYL TRIPEPTIDE-1; .ALPHA.-TOCOPHEROL ACETATE; NIACINAMIDE; CETOSTEARYL ALCOHOL; XANTHAN GUM; BUTYLENE GLYCOL; PROPANEDIOL; HOUTTUYNIA CORDATA FLOWERING TOP; EUCALYPTUS GLOBULUS LEAF; PENTYLENE GLYCOL; SODIUM ACETYLATED HYALURONATE; ACETYL HEXAPEPTIDE-8; PALMITOYL PENTAPEPTIDE-4; CENTELLA ASIATICA TRITERPENOIDS; BUTYLOCTYL SALICYLATE; SODIUM HYALURONATE; WATER; BEHENYL ACRYLATE POLYMER; HYDROXYACETOPHENONE; GLYCERIN; RESVERATROL; ETHYLHEXYLGLYCERIN; HYALURONIC ACID; AMMONIUM POLYACRYLOYLDIMETHYL TAURATE; ACETYL TYROSINE; BETULA ALBA JUICE; PHENOXYETHANOL; SODIUM STEAROYL GLUTAMATE; VINYLPYRROLIDONE/EICOSENE COPOLYMER; 1,2-HEXANEDIOL; PROLINE; ADENOSINE TRIPHOSPHATE

numbuzin 9 NAD BIO Super Defense Glow Sunscreen Broad Spectrum SPF 50

ACTIVE INGREDIENT

Avobenzone 3%, Homosalate 7%, Octisalate 5%, Octocrylene 5%

PURPOSE

Sunscreen

INDICATIONS AND USAGE

■ Helps prevent sunburn
■ If used as directed with other sun protection measures (see Directions), decreases the risk of skin cancer and early skin aging caused by the sun

INSTRUCTIONS FOR USE

■ Apply liberally 15 minutes before sun exposure
■ Children under 6 months: Ask a doctor
■ Reapply: ■ after 80 minutes of swimming or sweating ■ immediately after towel drying ■ at least every 2 hours
■ Sun Protection Measures. Spending time in the sun increases your risk of skin cancer and earty skin aging. To decrease this risk, regularly use a sunscreen with a Broad Spectrum SPF value of 15 or higher and other sun protection measures including: • Limit time in the sun, especially from 10 a.m.-2 p.m. • Wear long-sleeved shirts, pants, hats, and sunglasses

WARNINGS

For external use only

Do not use on damaged or broken skin

When using this product keep out of eyes. Rinse with water to remove.

Stop use and ask a doctor if rash occurs

Keep out of reach of children.
If swallowed, get medical help or contact a Poison Control Center right away.

protect the product in this container from excessive heat and direct sun

INACTIVE INGREDIENT

Water(Aqua), Butyloctyl Salicylate, Glycerin, Dimethicone, Poly C10-30 Alkyl Acrylate, VP/Eicosene Copolymer, Niacinamide, Ceteary Alcohol, Sodium Stearoyl Glutamate, Ammonium Polyacryloyldimethyl Taurate, Phenoxyethanol, Hydroxyacetophenone, Tocopheryl Acetate, Panthenol, Xanthan Gum, Allantoin, Hydrolyzed Collagen, Glycyrrhiza Glabra (Licorice) Root Extract, Butylene Glycol, Propanediol, 1,2-Hexanediol, Houttuynia Cordata Extract, Sodium Hyaluronate, Acetyl Tyrosine, Betula Alba Bark Extract, Centella Asiatica Extract, Resveratrol, Proline, Adenosine Triphosphate, Hydrolyzed Vegetable Protein, Nicotinamide Adenine Dinucleotide, Ethylhexylglycerin, Eucalyptus Globulus Leaf Extract, Polyglutamic Acid, Hyaluronic Acid, Hydrolyzed Hyaluronic Acid, Hydrolyzed Sodium Hyaluronate, Hydroxypropyltrimonium Hyaluronate, Potassium Hyaluronate, Sodium Hyaluronate Crosspolymer, Pentylene Glycol, Sodium Acetylated Hyaluronate, Acetyl Hexapeptide-8, Acetyl Octapeptide-3, Copper Tripeptide-1, Palmitoyl Pentapeptide-4, Palmitoyl Tetrapeptide-7, Palmitoyl Tripeptide-1, Tripeptide-1, Tripeptide-2, Tripeptide-3

QUESTIONS

cs_numbuzin@benow.co.kr

PACKAGE LABEL

numbuzin 9+

NAD+ + 9 Peptides

For All Skin

NAD+ BIO Super Defense Glow Sunscreen

Broad Spectrum SPF 50

50mL 1.9fl.oz